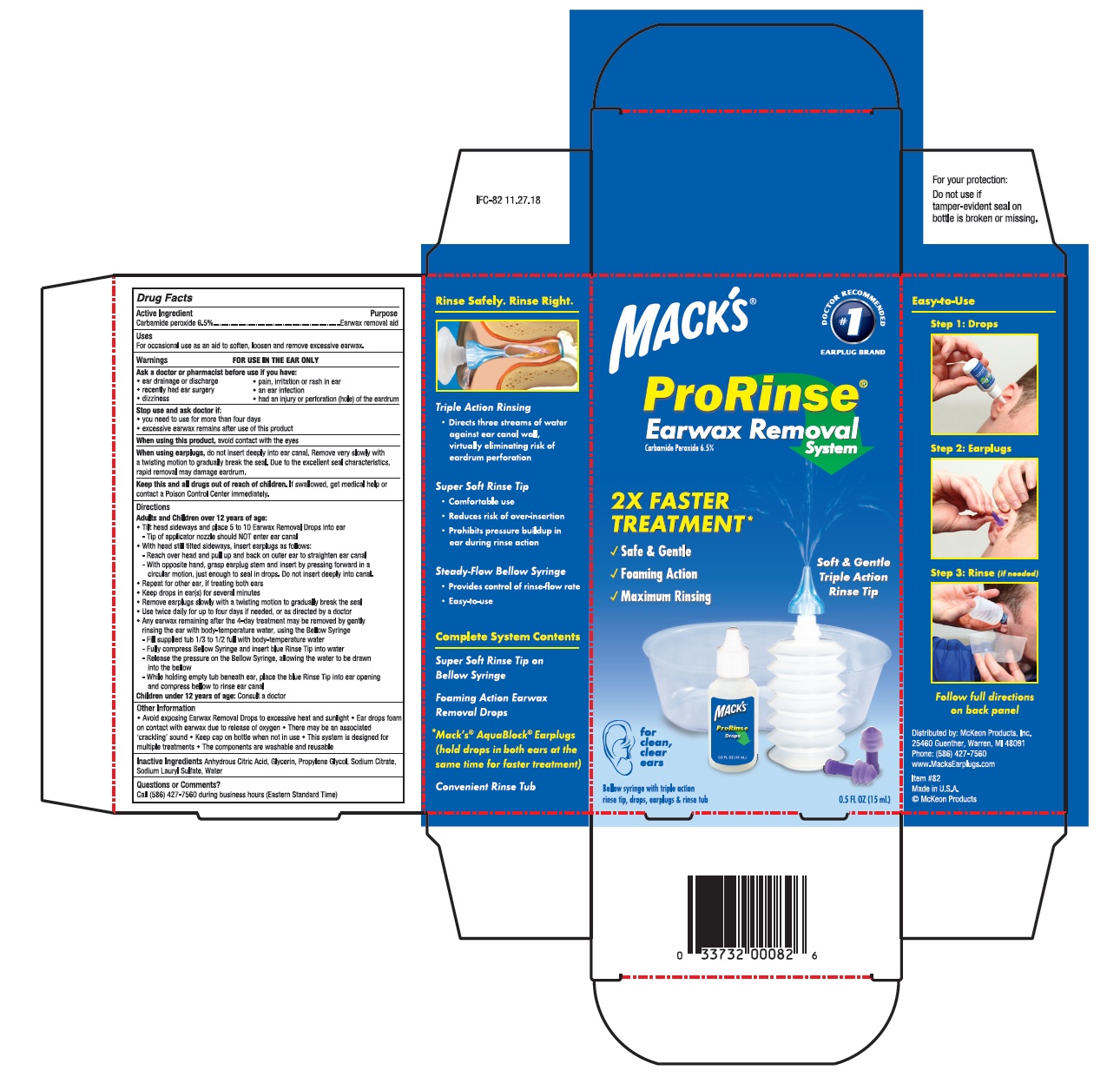 DRUG LABEL: ProRinse Earwax Removal System
NDC: 66354-007 | Form: SOLUTION/ DROPS
Manufacturer: McKeon Products Inc
Category: otc | Type: HUMAN OTC DRUG LABEL
Date: 20260209

ACTIVE INGREDIENTS: CARBAMIDE PEROXIDE 65 mg/1 mL
INACTIVE INGREDIENTS: ANHYDROUS CITRIC ACID; GLYCERIN; PROPYLENE GLYCOL; SODIUM CITRATE; SODIUM LAURYL SULFATE; WATER

Active ingredient

Carbamide peroxide 6.5%

Purpose

Earwax removal aid

Uses

for occasional use as an aid to soften, loosen, and remove excessive earwax

Warnings

For use in the ear only

Ask a doctor or pharmacist before use if you have:

- ear drainage or discharge
- recently had ear surgery
- dizziness
- pain, irritation, or rash in the ear
- an ear infection
- had an injury or perforation (hole) of the eardrum

Stop use and ask doctor if:

- you need to use for more than four days
- excessive earwax remains after use of this product

When using this product, avoid contact with the eyes

When using earplugs, do not insert deeply into ear canal. Remove very slowly with a twisting motion to gradually break the seal. Due to the excellent seal characteristics, rapid removal may damage eardrum

Keep this and all drugs out of reach of children. If swallowed, get medical help or contact a Poison Control Center immediately.

Directions

Adults and Children over 12 years of age:

- Tilt head sideways and place 5 to 10 Earwax Removal Drops into ear

Tip of applicator nozzle should NOT enter ear canal

- With head still sideways, insert earplugs as follows:

Reach over head and pull up and back on outer ear to straighten ear canal

With opposite hand, grasp earplug stem and insert by pressing forward in a circular motion, just enough to seal in drops. Do not insert deeply into canal.

- Repeat for other ear, if treating both ears
- Keep drops in ear(s) for several minutes
- Remove earplugs slowly with a twisting motion to gradually break the seal
- Use twice daily for up to four days if needed, or as directed by a doctor
- Any earwax remaining after the 4-day treatment may be removed by gently rinsing the ear with body-temperature water, using the Bellow Syringe

Fill supplied tub 1/3 to 1/2 full with body-temperature water

Fully compress Bellow Syringe and insert blue Rinse Tip into water

Release the pressure on the Bellow Syringe, allowing the water to be drawn into the bellow

While holding tub beneath ear, place the blue Rinse Tip into ear opening and compress bellow to rinse ear canal

Children under 12 years of age: Consult a doctor

Other information

- Avoid exposing Earwax Removal Drops to excessive heat and sunlight
- Ear drops foam on contact with earwax due to release of oxygen. There may be an associated “crackling” sound
- Keep cap on bottle when not in use
- This system is designed for multiple treatments
- The components are washable and reusable

Inactive ingredients

- anhydrous citric acid, glycerin, propylene glycol, sodium citrate, sodium lauryl sulfate, water

Questions or comments?

Call (586) 427-7560 during business hours (EST)